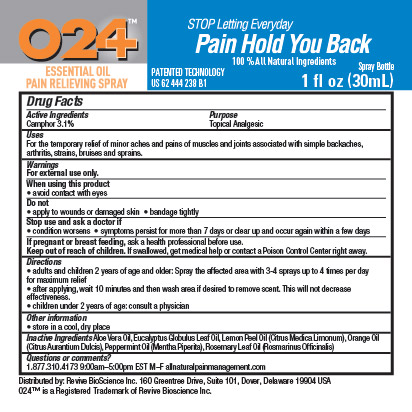 DRUG LABEL: O24
NDC: 76433-004 | Form: SPRAY
Manufacturer: Revive Bioscience, Inc.
Category: otc | Type: HUMAN OTC DRUG LABEL
Date: 20120126

ACTIVE INGREDIENTS: CAMPHOR (SYNTHETIC) 1 mL/30 mL
INACTIVE INGREDIENTS: EUCALYPTUS OIL; LEMON OIL; ORANGE OIL; PEPPERMINT OIL; ROSEMARY OIL

ACTIVE INGREDIENT

camphor 3.1%

PURPOSE

Topical Analgesic

INDICATIONS AND USAGE

For the temporary relief of minor aches and pains of muscles and joints associated with simple backaches, arthritis, strains, bruises and sprains.

WARNINGS

For external use only.

When using this product

- avoid contact with eyes

Do not

- apply to wounds or damaged skin
- bandage tightly

Stop use and ask a doctor if

- condition worsens
- symptoms persist for more than 7 days or clear up and occur again within a few days

PREGNANCY OR BREAST FEEDING

If pregnant or breast feeding, ask a health professional before use.

Keep out of reach of children. If swallowed, get medical help or contact a Poison Control Center right away.

Directions

- adults and children 2 years of age and older: Spray the affected area with 3-4 sprays up to 4 times per day for maximum relief
- after applying, wait 10 minutes and then wash area if desire to remove scent. This will not decrease effectiveness.
- children under 2 years of age: consult a physician

STORAGE AND HANDLING

store in a cool, dry place

INACTIVE INGREDIENT

Aloe Vera Oil, Eucalyptus Globulus Leaf Oil, Lemon Peel Oil (Citrus Medica Limonum), Orange Oil (Citrus Aurantium Dulcis), Peppermint Oil (Mentha Piperita), Rosemary Leaf Oil (Rosmarinus Officinalis)

Questions or comments?

1.877.310.4173 9:00am-5:00pm EST M-F

allnaturalpainmanagement.com